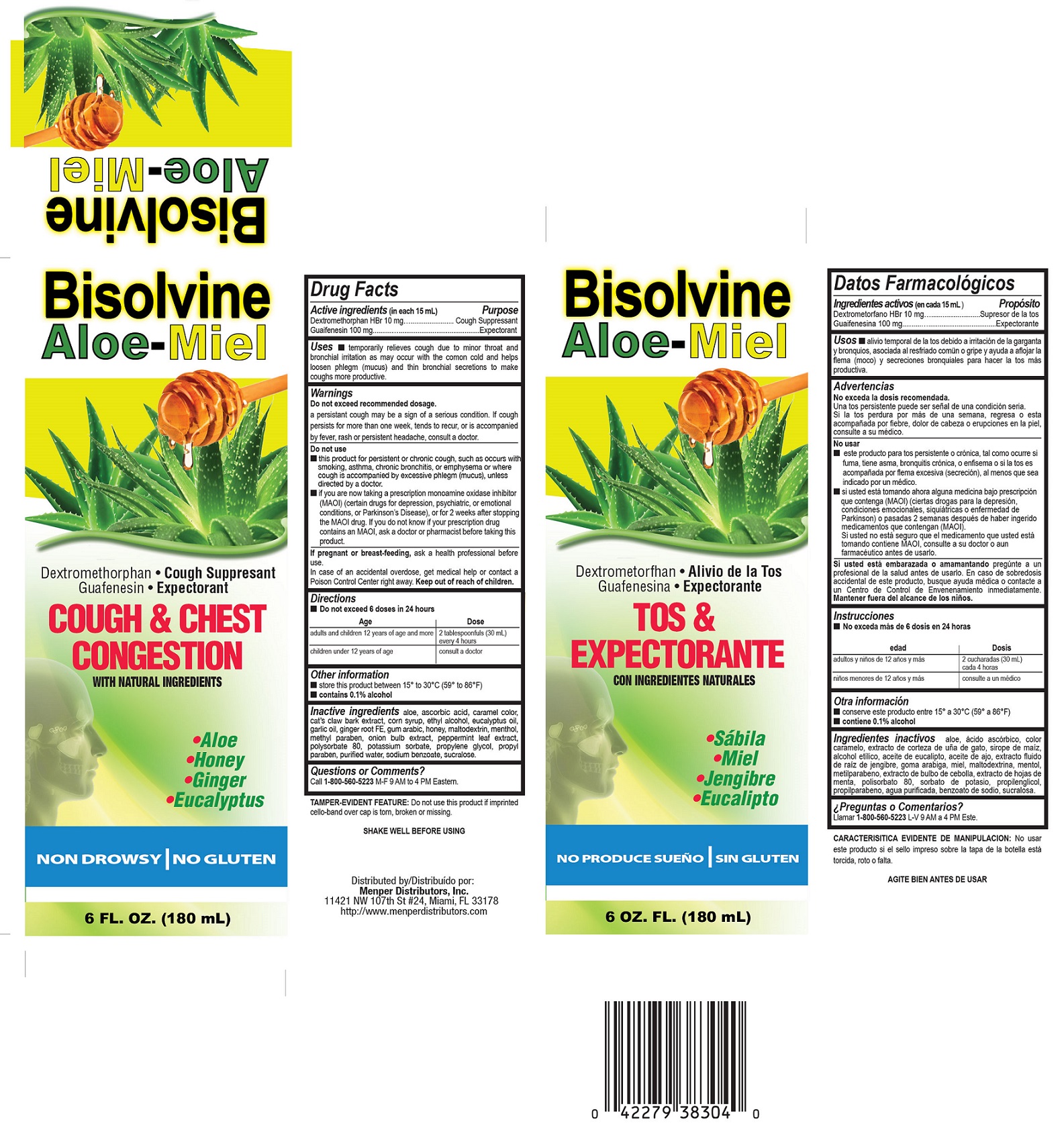 DRUG LABEL: Bisolvine
NDC: 53145-402 | Form: LIQUID
Manufacturer: MENPER DISTRIBUTORS INC.
Category: otc | Type: HUMAN OTC DRUG LABEL
Date: 20250722

ACTIVE INGREDIENTS: DEXTROMETHORPHAN HYDROBROMIDE 10 mg/15 mL; GUAIFENESIN 100 mg/15 mL
INACTIVE INGREDIENTS: ALOE; ASCORBIC ACID; CAT'S CLAW; CORN SYRUP; ALCOHOL; EUCALYPTUS OIL; GARLIC; GINGER; ACACIA; HONEY; MENTHOL; METHYLPARABEN; ONION; PEPPERMINT; POLYSORBATE 80; POTASSIUM SORBATE; PROPYLENE GLYCOL; PROPYLPARABEN; SODIUM BENZOATE; SUCRALOSE; SUNFLOWER OIL; WATER; DIACETYLTARTARIC AND FATTY ACID ESTERS OF GLYCEROL; CARAMEL

Bisolvine

Active Ingredients (in each 15 mL)

Dextromethorphan HBr 10mg............................ Cough Suppressant

Guaifenesin 100 mg ......................................... Expectorant

Purpose

Cough Suppressant

Expectorant

Uses

temporarily relieves cough due to minor throat and bronchial irritation as may occur with the common cold and helps loosen phlegm (mucus) and thin bronchial secretions to make coughs more productive.

Do not exceed recommended dosage.

A persistant cough may be a sign of serious condition, if cough persist for more than one week, tends to recur, or is accompanied by fever, rash or persistent headache, consult a doctor.

Do not use:

* this product for persistent or chronic cough, such as occurs with smoking, asthma, chronic bronchitis, or emphysema or where cough is accompanied by excessive phlegm (mucus), unless directed by a doctor.
* If you are now taking a prescription monoamine oxidase inhibitor (MAOI) (certain drugs for depression, psychiatric, or emotional conditions, or Parkinson's Disease), or for 2 weeks after stopping the MAOI drug. If you do not know if your prescription drug contains an MAOI, ask a doctor or pharmacist before taking this product.

KEEP OUT OF REACH OF CHILDREN

In case of accidental overdose, get medical help or contact a Poison Control Center right away. Keep out of reach of children

PREGNANCY OR BREAST FEEDING

If pregnant or breast-feeding, ask a health professional before use.

Directions

- Do not exceed 6 doses in 24 hours

Age | Dose
Adults and children 12 years of age and more | 2 teaspoonfuls (30 ml) every 4 hours
Children under 12 years of age | Consult your doctor

Inactive Ingredients

Aloe leaf extract, ascorbic acid, caramel color, cat's claw bark extract, corn syrup, DATEM, ethyl alcohol, eucalyptus oil, flavor, garlic bulb extract, ginger root extract, gum arabic, honey, menthol, methylparaben, onion bulb extract, peppermint leaf extract, polysorbate 80, potassium sorbate, propylene glycol, propylparaben, sodium benzoate, sucralose, sunflower oil, and water.

Questions or Coments?

Call 1-800-560-5223 M-F 9 AM to 4 PM Eastern.